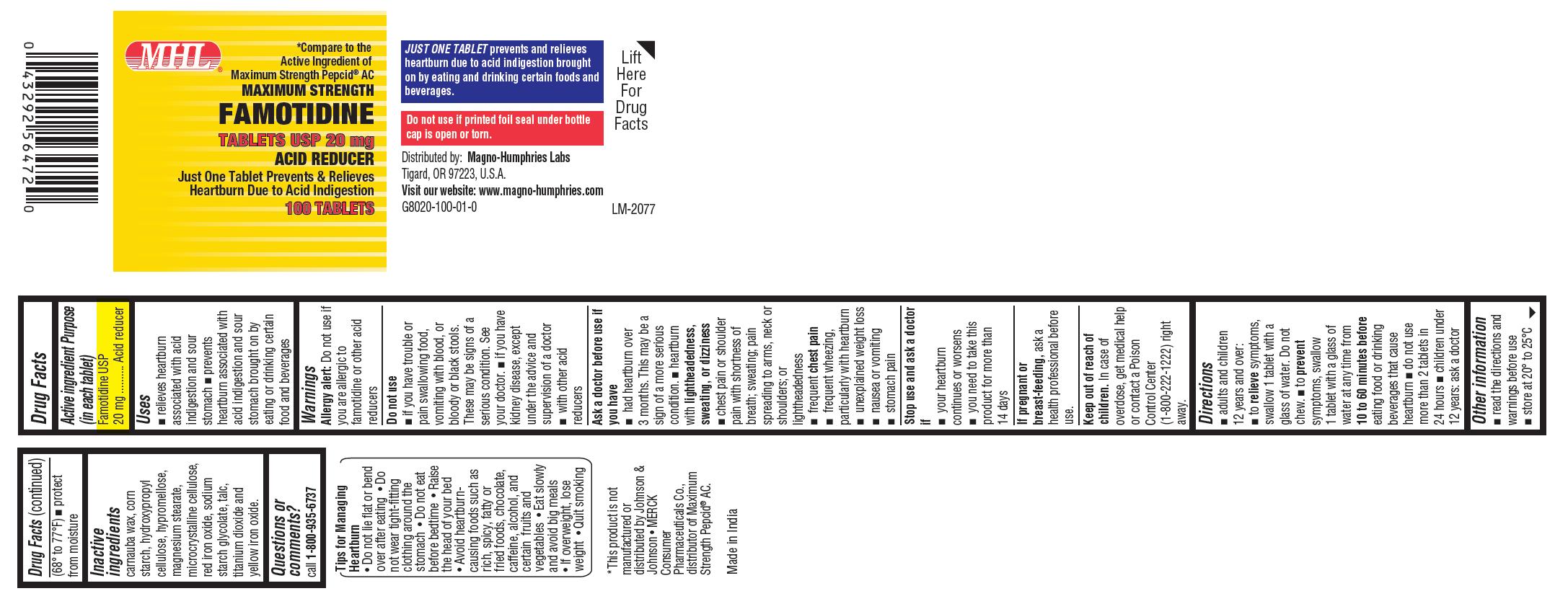 DRUG LABEL: Famotidine
NDC: 54257-802 | Form: TABLET, FILM COATED
Manufacturer: Magno-Humphries, Inc.
Category: otc | Type: Human OTC Drug Label
Date: 20250502

ACTIVE INGREDIENTS: FAMOTIDINE 20 mg/1 1
INACTIVE INGREDIENTS: CARNAUBA WAX; STARCH, CORN; HYDROXYPROPYL CELLULOSE (1600000 WAMW); HYPROMELLOSE 2910 (5 MPA.S); MAGNESIUM STEARATE; MICROCRYSTALLINE CELLULOSE; FERRIC OXIDE RED; SODIUM STARCH GLYCOLATE TYPE A CORN; TALC; TITANIUM DIOXIDE; FERRIC OXIDE YELLOW

Drug Facts

Active ingredient (in each tablet)

Famotidine USP 20 mg

Purpose

Acid reducer

Uses

- relieves heartburn associated with acid indigestion and sour stomach
- prevents heartburn associated with acid indigestion and sour stomach brought on by eating or drinking certain food and beverages

Warnings

Allergy alert: Do not use if you are allergic to famotidine or other acid reducers

Do not use

- if you have trouble or pain swallowing food, vomiting with blood, or bloody or black stools. These may be signs of a serious condition. See your doctor.
- if you have kidney disease, except under the advice and supervision of a doctor
- with other acid reducers

Ask a doctor before use if you have

- had heartburn over 3 months. This may be a sign of a more serious condition.
- heartburn with lightheadedness, sweating, or dizziness
- chest pain or shoulder pain with shortness of breath; sweating; pain spreading to arms, neck or shoulders; or lightheadedness
- frequent chest pain
- frequent wheezing, particularly with heartburn
- unexplained weight loss
- nausea or vomiting
- stomach pain

Stop use and ask a doctor if

- your heartburn continues or worsens
- you need to take this product for more than 14 days

If pregnant or breast-feeding,

ask a health professional before use.

Keep out of reach of children.

In case of overdose, get medical help or contact a Poison Control Center (1-800-222-1222) right away.

Directions

- adults and children 12 years and over:
  - to relieve symptoms, swallow 1 tablet with a glass of water. Do not chew.
  - to prevent symptoms, swallow 1 tablet with a glass of water at any time from 10 to 60 minutes before eating food or drinking beverages that cause heartburn
  - do not use more than 2 tablets in 24 hours
- children under 12 years: ask a doctor

Other information

• read the directions and warnings before use
• store at 20° to 25°C (68° to 77°F)
• protect from moisture

Inactive ingredients

carnauba wax, corn starch, hydroxypropyl cellulose, hypromellose, magnesium stearate, microcrystalline cellulose, red iron oxide, sodium starch glycolate, talc, titanium dioxide and yellow iron oxide.

Questions or comments?

call 1-800-935-6737
Tips for Managing Heartburn

- Do not lie flat or bend over after eating
- Do not wear tight-fitting clothing around the stomach
- Do not eat before bedtime
- Raise the head of your bed
- Avoid heartburn-causing foods such as rich, spicy, fatty or fried foods, chocolate, caffeine, alcohol, and certain fruits and vegetables
- Eat slowly and avoid big meals
- If overweight, lose weight
- Quit smoking

JUST ONE TABLET prevents and relieves heartburn due to acid indigestion brought on by eating and drinking certain foods and beverages.
Do not use if printed foil seal under bottle cap is open or torn.

Distributed by:
Magno-Humphries Labs
Tigard, OR 97223, U.S.A.
Visit our website: www.magno-humphries.com
Made in India

PACKAGE LABEL-PRINCIPAL DISPLAY PANEL -20 mg (100 Tablets, Container Label)

MHL℗
*Compare to the Active Ingredient
of Maximum Strength Pepcid® AC
MAXIMUM STRENGTH
FAMOTIDINE
TABLETS USP 20 mg
ACID REDUCER
Just One Tablet Prevents & Relieves
Heartburn Due to Acid Indigestion
100 TABLETS